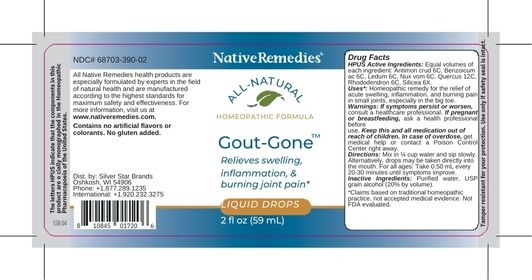 DRUG LABEL: NativeRemedies Gout-Gone
NDC: 68703-390 | Form: LIQUID
Manufacturer: Silver Star Brands
Category: homeopathic | Type: HUMAN OTC DRUG LABEL
Date: 20250101

ACTIVE INGREDIENTS: SILICON DIOXIDE 6 [hp_X]/59 mL; ANTIMONY TRISULFIDE 6 [hp_C]/59 mL; BENZOIC ACID 6 [hp_C]/59 mL; QUERCUS ROBUR FLOWER 12 [hp_C]/59 mL; STRYCHNOS NUX-VOMICA SEED 6 [hp_C]/59 mL; RHODODENDRON AUREUM LEAF 6 [hp_C]/59 mL; LEDUM PALUSTRE TWIG 6 [hp_C]/59 mL
INACTIVE INGREDIENTS: ALCOHOL; WATER

NativeRemedies® Gout-Gone™

HPUS Active Ingredients: Equal volumes of each ingredient: Antimon crud 6C, Benzoicum ac 6C, Ledum 6C, Nux vom 6C, Quercus 12C, Rhododendron 6C, Silicea 6X.

The letters HPUS indicate that the components in this product are officially monographed in the Homeopathic Pharmacopoeia of the United States.

Uses*:

Uses*: Homeopathic remedy for the relief of acute swelling, inflammation, and burning pain in small joints, especially in the big toe.

*Claims based on traditional homeopathic practice, not accepted medical evidence. Not FDA evaluated.

Warnings

Warnings: If symptoms persist or worsen, consult a healthcare professional. If pregnant or breastfeeding, ask a health professional before use. Keep this and all medication out of reach of children. In case of overdose, get medical help or contact a Poison Control Center right away.

Directions

Directions: Mix in 1/4 cup water and sip slowly. Alternatively, drops may be taken directly into the mouth. For all ages: Take 0.50 mL every 20-30 minutes until symptoms improve.

OTHER SAFETY INFORMATION

Contains no artificial flavors or colorants. No gluten added.

Tampler resistant for your protection. Use only if safety seal is intact.

Inactive Ingredients

Inactive Ingredients: Purified water, USP grain alcohol (20% of volumn).

KEEP OUT OF REACH OF CHILDREN

Keep this and all medications out of reach of children.

PREGNANCY OR BREAST FEEDING

If pregnant or breastfeeding, ask a health professional before use.

PURPOSE

Relieves swelling, inflammation, & buring joint pain.